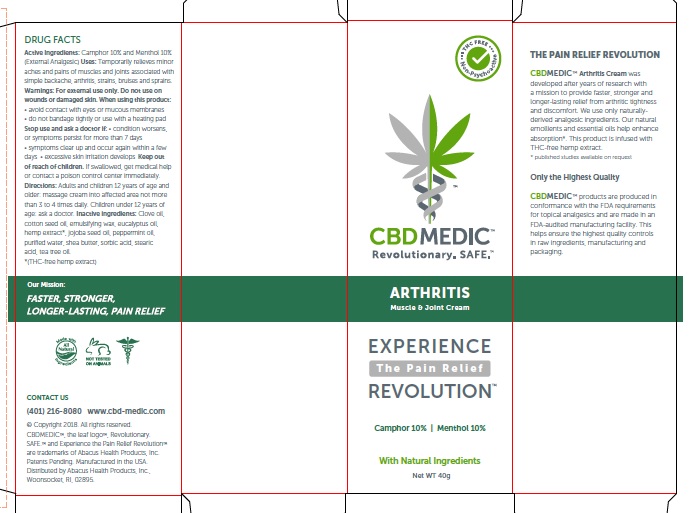 DRUG LABEL: CBDMEDIC Arthritis Pain Relief
NDC: 24909-728 | Form: CREAM
Manufacturer: AIDANCE SKINCARE & TOPICAL SOLUTIONS, LLC
Category: otc | Type: HUMAN OTC DRUG LABEL
Date: 20181128

ACTIVE INGREDIENTS: CAMPHOR (SYNTHETIC) 100 mg/1 g; MENTHOL 100 mg/1 g
INACTIVE INGREDIENTS: CLOVE OIL; COTTONSEED OIL; CETOSTEARYL ALCOHOL; EUCALYPTUS OIL; HEMP; JOJOBA OIL; PEPPERMINT OIL; WATER; SHEA BUTTER; SORBIC ACID; STEARIC ACID; TEA TREE OIL

CBDMEDIC Arthritis Pain Relief

Active Ingredients and Purpose

Active Ingredients: Camphor 10%, Menthol 10% (External Analgesics)

Uses

Temporarily relieves minor aches and pains of muscles and joints associated with simple backache, arthritis, strains, bruises and sprains.

Warnings

Warnings: For external use only. Do not use on wounds or damaged skin. When using this product: • avoid contact with eyes or mucous membranes • do not bandage tightly or use with a heating pad. Stop use and ask a doctor if: • condition worsens, or symptoms persist for more than 7 days • symptoms clear up and occur again within a few days • excessive skin irritation develops.

Keep out of reach of children

If swallowed, get medical help or contact a poison control center immediately.

Directions

Adults and children 12 years of age and older: massage cream into affected area not more than 3 to 4 times daily. Children under 12 years of age: ask a doctor.

Inactive ingredients

Clove oil, cotton seed oil, emulsifying wax, eucalyptus oil, hemp extrct*, jojoba seed oil, peppermint oil, purified water, shea butter, sorbic acid,

stearic acid, tea tree oil.